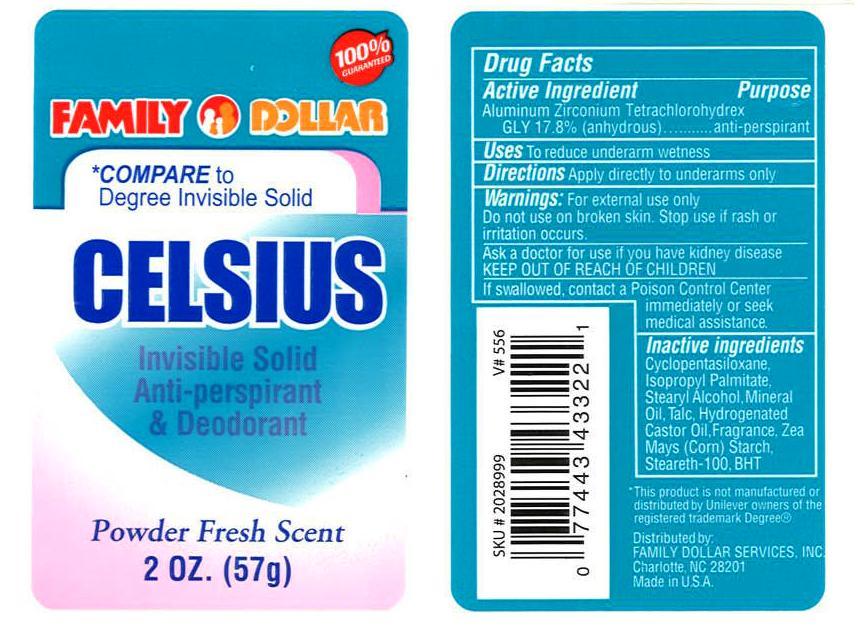 DRUG LABEL: Family Dollar Celsius
NDC: 10889-102 | Form: STICK
Manufacturer: VVF Kansas Services LLC
Category: otc | Type: HUMAN OTC DRUG LABEL
Date: 20090930

ACTIVE INGREDIENTS: aluminum zirconium tetrachlorohydrex gly 17.8 1/1 1

Family Dollar Celsius (Aluminun Zirconium Tetrachlorohydrex Gly)

ACTIVE INGREDIENT

Aluminum Zirconium Tetrachlorohydrex Gly 17.8%

PURPOSE

To reduce underarm wetness

USES

Apply directly to underarms only

WARNINGS

For external use only.

Do not use on broken skin. Stop use if rash or irritation occurs.

Ask a doctor if you have kidney disease

KEEP OUT OF REACH OF CHILDREN

If swallowed, contact a Poison Control Center immediately or seek medical attention.

INACTIVE INGREDIENTS

Cyclopentasiloxane, Isopropyl Palmitate, Stearyl Alcohol, Mineral Oil, Talc, Hydrogenated Castor Oil, Fragrance, Zea Mays (corn) Starch, Steareth-100, BHT

* This product is not manufactured or distributed by Unilever owners of the registered trademark Degree (R)
Distributed by:
FAMILY DOLLAR SERVICES, INC.
Charlotte, NC 28201
Made in USA

PRODUCT LABEL

100% Guaranteed

Family Dollar

*Compare to Degree Invisible Solid

CELSIUS

Invisible Solid Antiperspirant and Deodorant

Powder Fresh Scent

2 OZ. (57g)